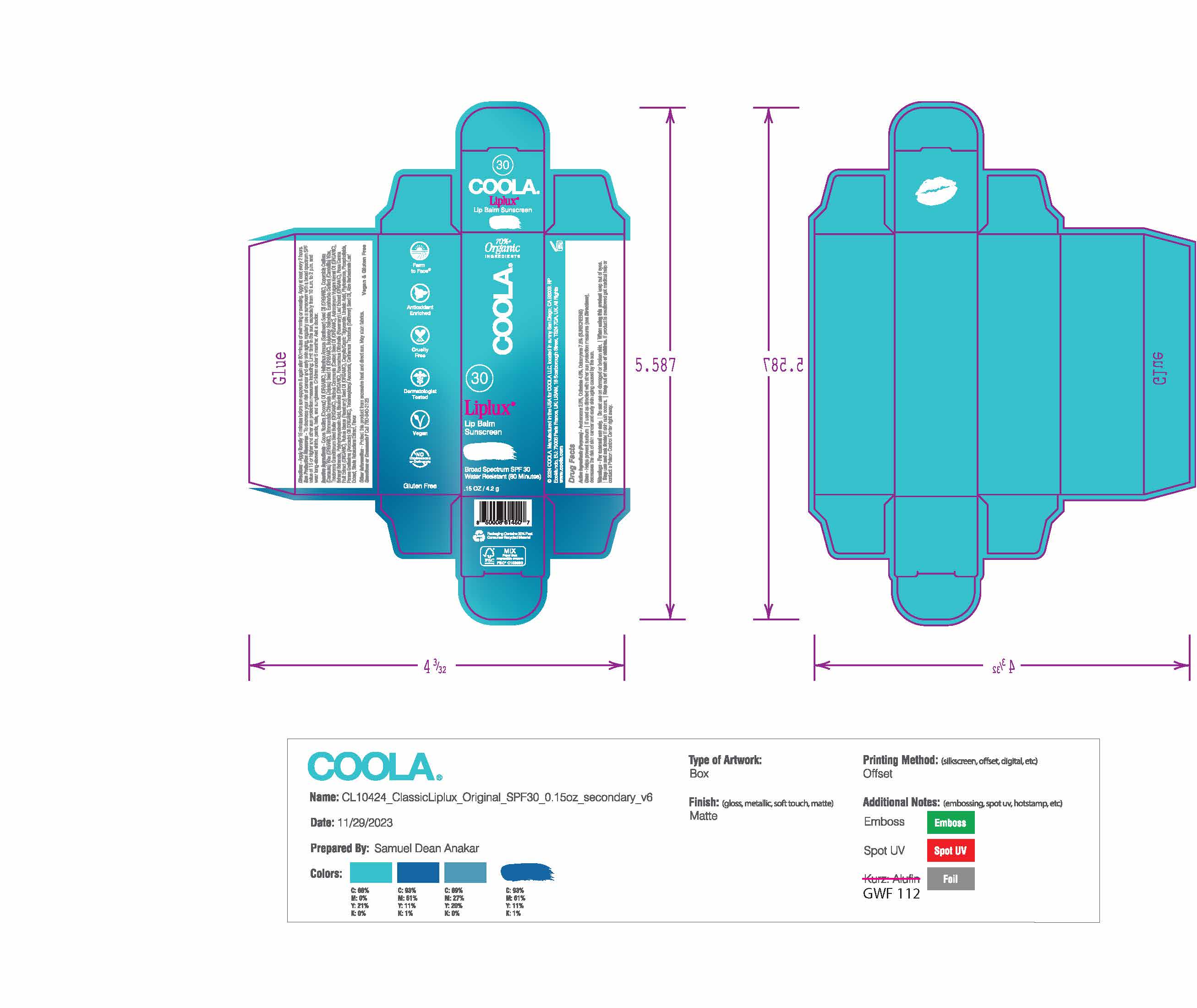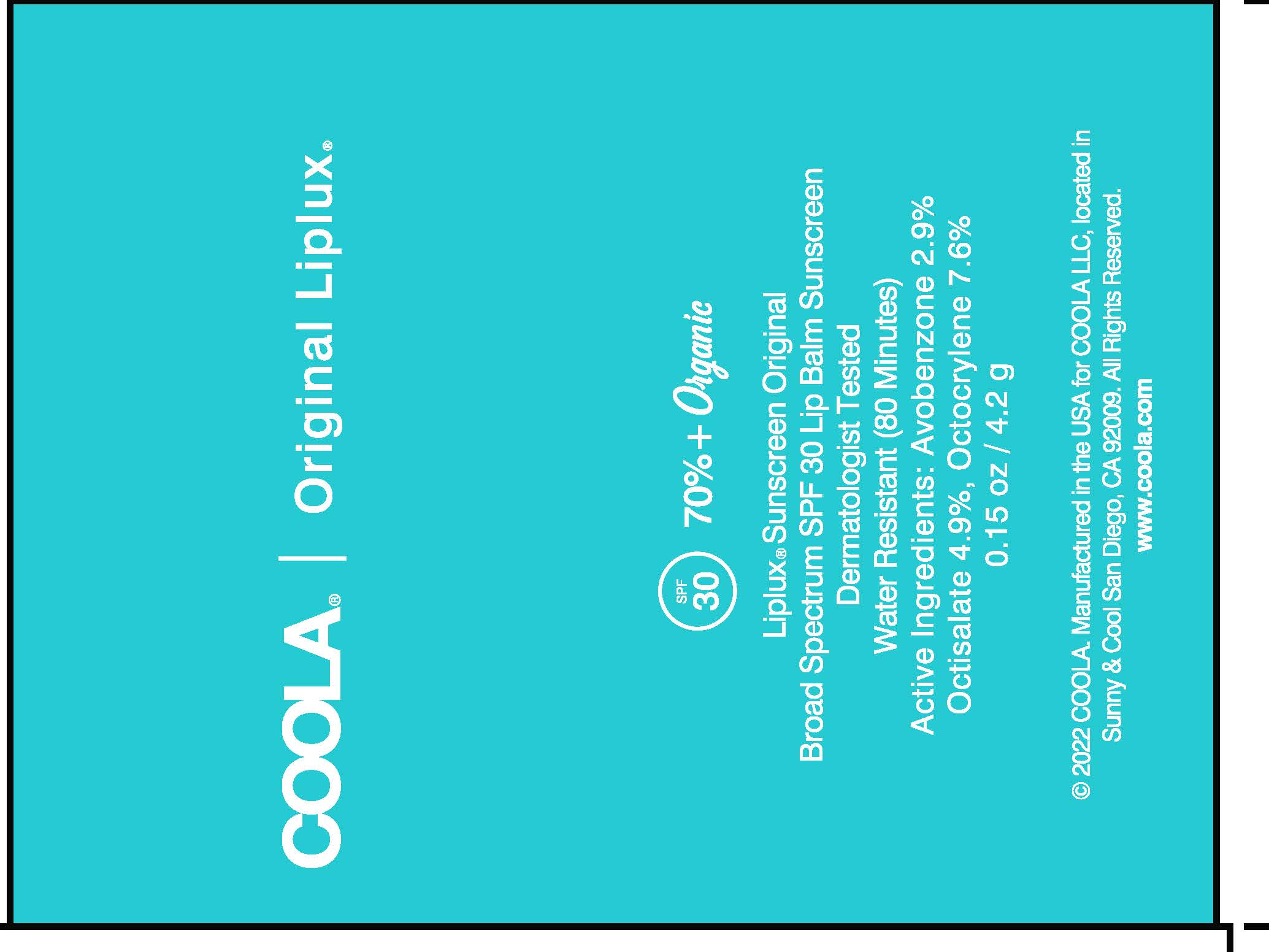 DRUG LABEL: Liplux
NDC: 79753-012 | Form: STICK
Manufacturer: COOLA LLC
Category: otc | Type: HUMAN OTC DRUG LABEL
Date: 20250217

ACTIVE INGREDIENTS: OCTISALATE 5 g/100 g; OCTOCRYLENE 8 g/100 g; AVOBENZONE 3 g/100 g
INACTIVE INGREDIENTS: LINOLEIC ACID; SAFFLOWER OIL; ASTROCARYUM VULGARE KERNEL OIL; COCONUT OIL; BEHENYL BEHENATE; POLYHYDROXYSTEARIC ACID STEARATE; CANDELILLA WAX; THEOBROMA GRANDIFLORUM SEED BUTTER; CARNAUBA WAX; SUNFLOWER OIL; TOCOPHEROL; AVOCADO OIL; ALOE VERA LEAF; REBAUDIOSIDE A; JOJOBA OIL; CASTOR OIL; ROSEMARY; ROSA CANINA FRUIT; LEVOMENOL; MEDIUM-CHAIN TRIGLYCERIDES; BUTYLOCTYL SALICYLATE; RASPBERRY SEED OIL

COOLA Classic Liplux Lip Balm SPF30 0.15oz - Original

Active Ingredients

Avobenzone 2.9%, Octisalate 4.9%, Octocrylene 7.6%

Purpose

Sunscreens

Uses

Helps prevent sunburn

If used as directed with other sun protection measures (see Directions), decreases the risk of skin cancer and early skin aging caused by the sun.

Warnings

For external use only.

Do not use on damaged or broken skin.

When using this product keep out of eyes.

Stop use and ask doctor if skin rash occurs.

Keep out of reach of children. If product is swallowed get medical help or contact a Poison Control Center right away.

Directions

Apply liberally 15 minutes before sun exposure & again after 80 minutes of swimming or sweating. Apply at least every 2 hours. Sun Protection Measures - to decrease your risk of cancer and early skin aging, regularly use a sunscreen wtih a broad spectrum SPF value of 15 or higher and other sun protection measures including: Limit time in the sun, expecially from 10 a.m. to 2 p.m. and wear long-sleeved shirts, paints, hats, and sunglasses. Children under 6 months: ask a doctor.

RECENT MAJOR CHANGES

correct spelling mistakes

Inactive ingredients

Aloe Barbadensis Leaf Extract, Astrocaryum Vulgare Kernel Oil (ORGANIC), Behenyl Behenate, Bisabolol, Butyloctyl Salicylate, Caprylic/Capric Triglyceride, Carthamus Tinctorius (Safflower) Seed Oil, Cocos Nucifera (Coconut) Oil (ORGANIC), Copernicia Cerifera (Carnauba) Wax (ORGANIC), Euphorbia Cerifera (Candelilla) Wax, Flavor, Helianthus Annuus (Sunflower) Seed Oil (ORGANIC), Linoleic Acid, Persea Gratissima (Avocado) Oil (Organic), Phospholipids, Phytosterols, Polyhydroxstearic Acid, Rubus Idaeus (Raspberry) Seed Oil (ORGANIC), Simmondsia Chinensis (Jojoba) Seed OIl (ORGANIC), Stevia Rebaudiana Extract, Tetrahexyldecyl Ascorbate, Theobroma Grandiflorum Seed Butter (ORGANIC), Tocopherol (ORGANIC)

Other Information

Protect this product from excessive heat and direct sun.

Questions or Concerns?

Call 760-940-2125